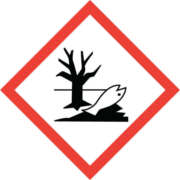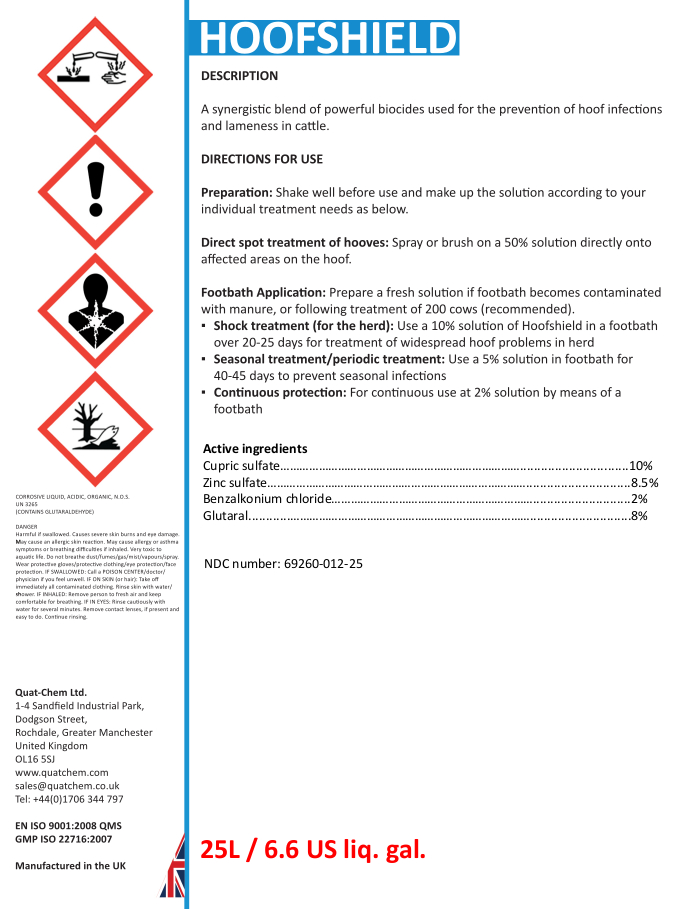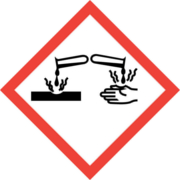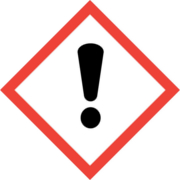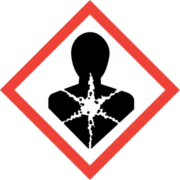 DRUG LABEL: Hoofshield
NDC: 69260-012 | Form: LIQUID
Manufacturer: Quat-Chem Ltd.
Category: animal | Type: OTC ANIMAL DRUG LABEL
Date: 20160718

ACTIVE INGREDIENTS: CUPRIC SULFATE 100 g/1 L; ZINC SULFATE 85 g/1 L; BENZALKONIUM CHLORIDE 20 g/1 L; GLUTARAL 80 g/1 L

Hoofshield